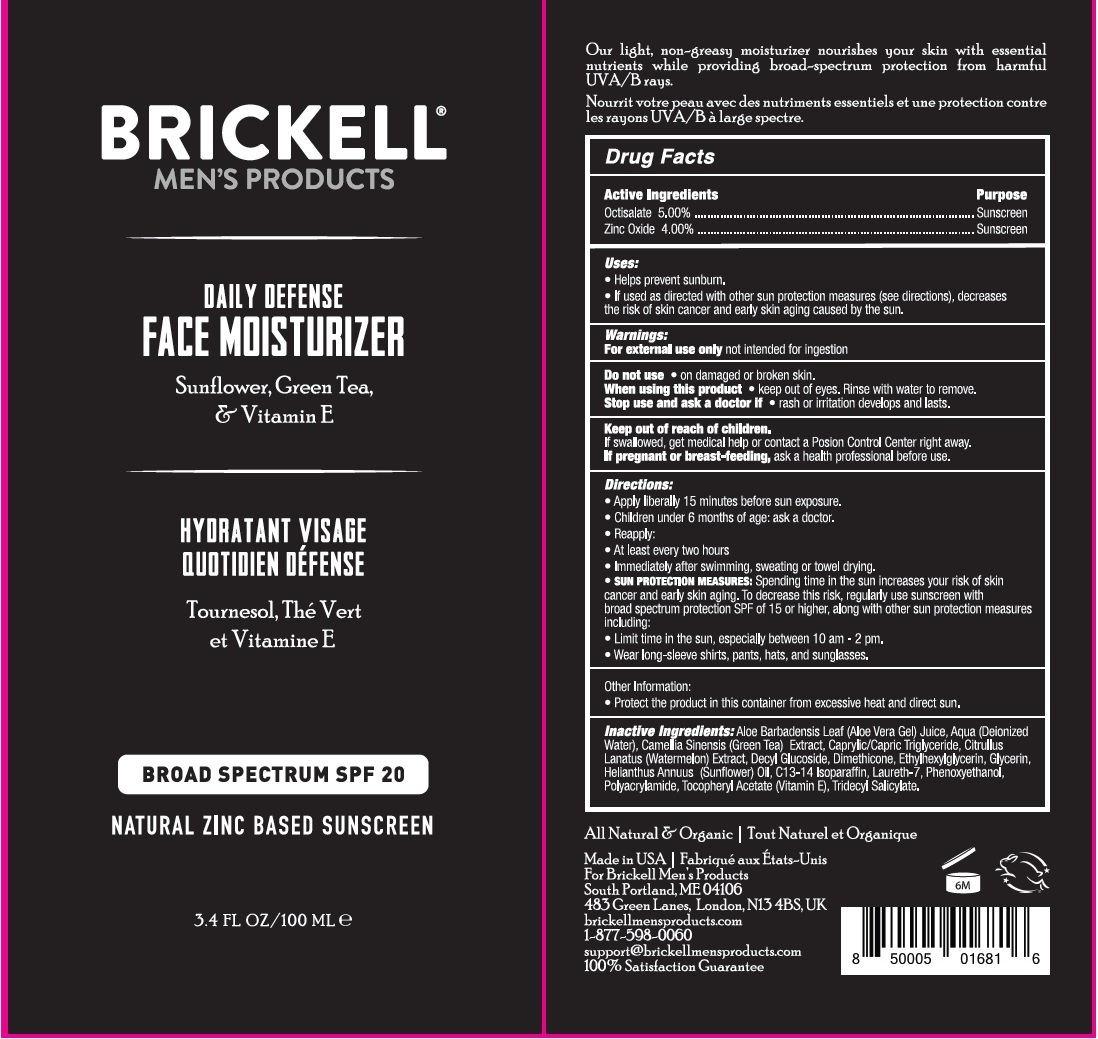 DRUG LABEL: Brickell Mens Products Daily Defense Face Moisturizer SPF-20
NDC: 82247-421 | Form: CREAM
Manufacturer: BRICKELL BRANDS LLC
Category: otc | Type: HUMAN OTC DRUG LABEL
Date: 20231111

ACTIVE INGREDIENTS: OCTISALATE 50 mg/1 mL; ZINC OXIDE 40 mg/1 mL
INACTIVE INGREDIENTS: ALOE VERA LEAF; WATER; GREEN TEA LEAF; MEDIUM-CHAIN TRIGLYCERIDES; WATERMELON; DECYL GLUCOSIDE; DIMETHICONE; ETHYLHEXYLGLYCERIN; GLYCERIN; SUNFLOWER OIL; C12-14 ISOPARAFFIN; LAURETH-7; PHENOXYETHANOL; .ALPHA.-TOCOPHEROL ACETATE; TRIDECYL SALICYLATE

Brickell Men's Products Daily Defense Face Moisturizer SPF-20

Active Ingredients

Octisalate 5.00%

Zinc Oxide 4.00

Purpose

Sunscreen

Uses:

• Helps prevent sunburn. • If used as directed with other sun protection measures (see directions), decreases the risk of skin cancer and early skin aging caused by the sun.

Warnings:

not intended for ingestion For external use only

Do not use

- on damaged or broken skin.

When using this product

- keep out of eyes. Rinse with water to remove.

Stop use and ask a doctor if

- rash or irritation develops and lasts.

Keep out of reach of children.

If swallowed, get medical help or contact a Poison Control Center right away.

If pregnant or breast-feeding,

ask a health professional before use.

Directions:

- Apply liberally 15 minutes before sun exposure.
- Children under 6 months of age: Ask a doctor.
- Reapply:
- At least every two hours
- Immediately after swimming, sweating or towel drying.
- Spending time in the sun increases your risk of skin cancer and early skin aging. To decrease this risk, regularly use sunscreen with a broad Spectrum protection SPF of 15 or higher, along with other sun protection measures including: SUN PROTECTION MEASURES:
- Limit time in the sun, especially from 10 a.m. – 2 p.m.
- Wear long-sleeve shirts, pants, hats, and sunglasses.

Other Information:

- Protect the product in this container from excessive heat and direct sun.

Inactive Ingredients:

Aloe Barbadensis Leaf (Aloe Vera Gel)Juice, Aqua (Deionized Water), Camellia Sinensis (Green Tea) Extract, Caprylic/Capric Triglyceride, Citrullus Lanatus(Watermelon) Extract, Decyl Glucoside, Dimethicone, Ethylhexylglycerin, Glycerin, Helianthus Annuus (Sunflower) Oil, C12-14Isoparaffin, Laureth-7, Phenoxyethanol, Polyacrylamide, Tocopheryl Acetate (Vitamin E), Tridecyl Salicylate.